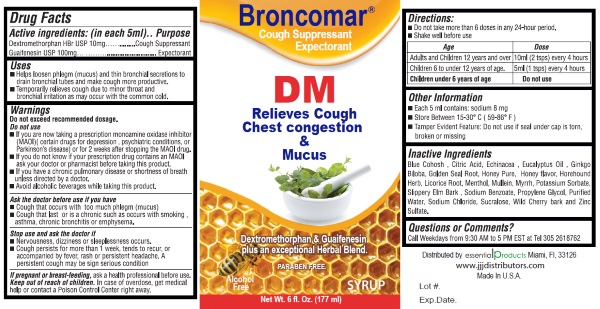 DRUG LABEL: Broncomar
NDC: 70242-101 | Form: LIQUID
Manufacturer: Dannso Corp./d.b.a. Essential Products
Category: otc | Type: HUMAN OTC DRUG LABEL
Date: 20160101

ACTIVE INGREDIENTS: DEXTROMETHORPHAN HYDROBROMIDE 10 mg/5 mL; GUAIFENESIN 100 mg/5 mL
INACTIVE INGREDIENTS: CAULOPHYLLUM THALICTROIDES ROOT; CITRIC ACID MONOHYDRATE; ECHINACEA; EUCALYPTUS OIL; GINKGO; GOLDENSEAL; HONEY; HOREHOUND; LICORICE; MENTHOL; VERBASCUM THAPSUS; MYRRH; POTASSIUM SORBATE; ULMUS RUBRA BARK; SODIUM BENZOATE; PROPYLENE GLYCOL; WATER; SODIUM CHLORIDE; SUCRALOSE; PRUNUS SEROTINA BARK; ZINC SULFATE

Broncomar DM

Active Ingredients:(in each 5 ml.) | Purpose
Dextromethorphan Hydrobromide 10 mg .................... | Cough Suppressant
Guaifenesin 100 mg....................................................... | Expectorant

Uses:

- Helps loosen phlegm (mucus) and thin bronchial secretions to drain bronchial tubes and make cough more productive.
- Temporarily relieves cough due to minor throat and bronchial irritation as may occur with the common cold.

Warnings

Do not exceed recommended dosage

Do not use

- If you are now taking a prescription monoamine oxidase inhibitor (MAOI) (certain drugs for depression, psychiatric conditions, or Parkison's disease) or for 2 weeks after stopping MAOI drug.
- If you do not know if your prescription drug contains MAOI as your doctor or pharmacist before taking this product.
- If you have a chronic pulmonary disease or shortness of breath unless directed by a doctor.
- Avoid alcoholic beverage while taking this product.

Stop use and ask a doctor

- Nervousness, dizziness or sleeplessness occurs.
- Cough persists more than 1 week, tends to recur or is accompanied by a fever, rash or persistent headache. A persistent cough may be signserious condition.

Ask doctor before use if you have

- Cough that occurs with too much phlegm(mucus)
- Cough that last or is a chronic such as occurs with smoking, asthma, chronic bronchitis or emphysema.

PREGNANCY OR BREAST FEEDING

If pregnant or breast-feeding ask a health professional before use.

Keep out of reach of children.

In case of overdose, get medical help or contact a Poison Control Center right away.

Directions

- Do not exceed 6 doses in any 24 hour period.
- Shake well before use.

AGE | DOSE
Adults and Children 12 years and over | 10 ml (2 tsps) every 4 hours
Children 6 to under 12 years of age | 5 ml (1 tsp) every 4 hours
Children under 6 years of age | Do not use

Other Information:

- Each 5 mls contains: sodium 8 mg
- Store between 15 - 30 degrees Celsius (59 - 86 Fahrenheit).
- Tamper Evident Feature:Do not use if seal under cap is torn, broken or missing.

Inactive Ingredient

Blue Cohosh , Citric Acid, Echinacea , Eucalyptus Oil , Ginkgo Biloba, Golden Seal Root, Honey Pure, Honey flavor, Horehound Herb, Licorice Root, Menthol, Mullein, Myrrh, Potassium Sorbate, Slippery Elm Bark , Sodium Benzoate, Propylene Glycol, Purified Water, Sodium Chloride, Sucralose, Wild Cherry bark and Zinc Sulfate.

Questions or Comments

Call Weekdays from 9:30 AM to 5PM EST at Tel 305-261-762

Distributed by

Essential Products Miami FL 33126

www.jjjdistributors.com

Made in U.S.A.